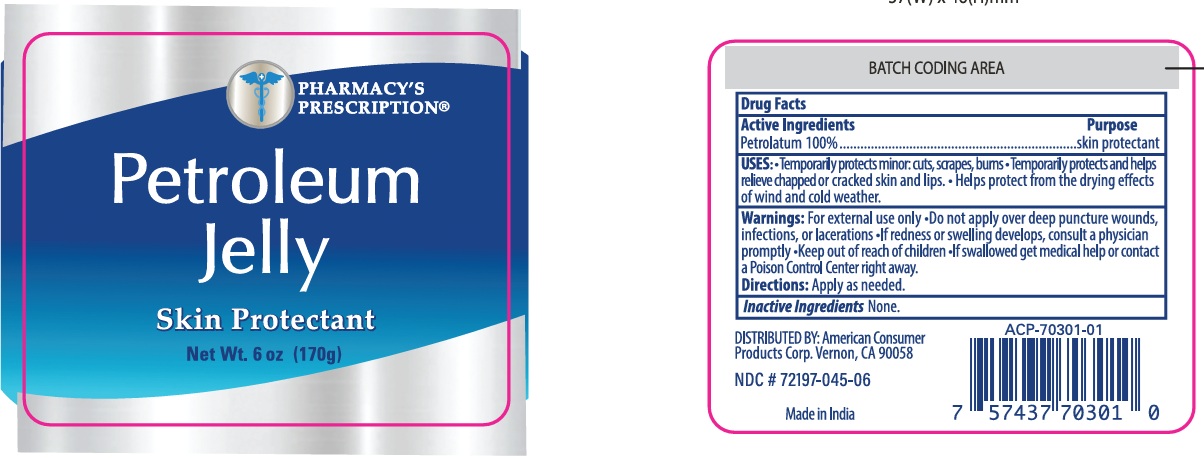 DRUG LABEL: PHARMACYS PRESCRIPTION PETROLEUM
NDC: 85891-012 | Form: JELLY
Manufacturer: SPARROW LIFE CARE PRIVATE LIMITED
Category: otc | Type: HUMAN OTC DRUG LABEL
Date: 20251212

ACTIVE INGREDIENTS: PETROLATUM 100 g/100 g

Active Ingredient Purpose

Petrolatum 100% Skin Protectant

Uses

- Temporarily protects minor cuts, scrapes, and burns.
- Temporarily protects and helps relieve chapped or cracked skin and lips.
- Helps protect from the drying effects of wind and cold weather.

Warnings

- For external use only.
- Do not apply over deep puncture wounds, infections, or lacerations.
- If redness or swelling develops, consult a physician promptly.
- Keep Out of Reach of Children. If swallowed, get medical help or contact a Poison Control Center right away.

Directions

Apply as needed.

Inactive ingredients

None